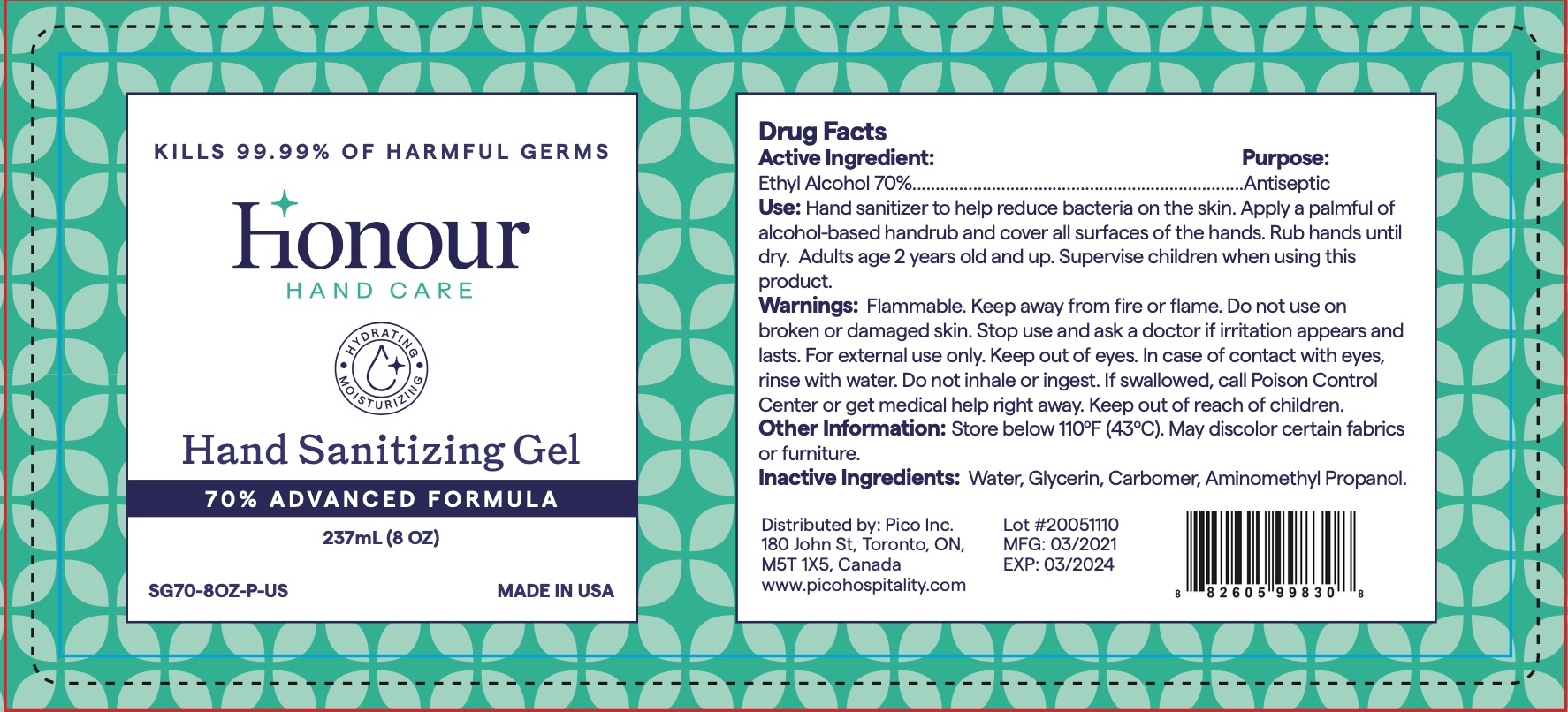 DRUG LABEL: Honour Hand Care Hand Sanitizing Gel
NDC: 78082-024 | Form: GEL
Manufacturer: PICO Inc.
Category: otc | Type: HUMAN OTC DRUG LABEL
Date: 20211217

ACTIVE INGREDIENTS: ALCOHOL 165.9 mL/237 mL
INACTIVE INGREDIENTS: CARBOMER INTERPOLYMER TYPE A (ALLYL SUCROSE CROSSLINKED); GLYCERIN; AMINOMETHYLPROPANOL; WATER

Honour Hand Care Hand Sanitizing Gel 237 ml

Active Ingredient

Ethyl alcohol 70%

Purpose

Antiseptic

Uses

For hand sanitizing to decrease bacterial on the skin.

Warnings

Flammable, keep away from fire or flame

For external use only.

Do not use

on damaged, inflamated, or broken skin.

When using this product

avoid contact with eyes. In case of contact with eyes, rinse thoroughly with water.

Stop use and ask a doctor

if irritation and rendess develops and lasts for more than 72 hours.

Keep out of reach of children.

If swallowed, get medical help or contact a Poison Control Center right away.

Directions

Wet hands throughly with product, allow to dry without wiping.

Inactive Ingredients

glycerin, carbomer, water, aminomethyl propanol

Questions?

1-800-258-7426

Package Labeling:

237 ml NDC 78082-024-01